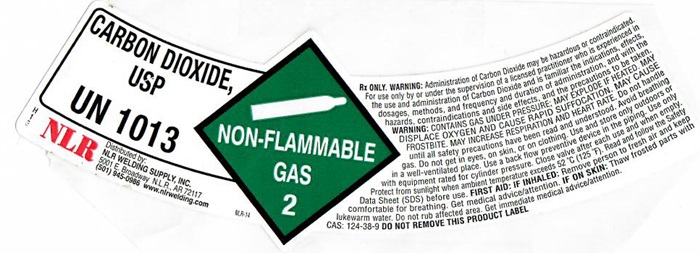 DRUG LABEL: CARBON DIOXIDE
NDC: 62045-7333 | Form: GAS
Manufacturer: NLR Welding Supply, Inc.
Category: prescription | Type: HUMAN PRESCRIPTION DRUG LABEL
Date: 20231108

ACTIVE INGREDIENTS: CARBON DIOXIDE 99 L/100 L

Carbon Dioxide

CARBON DIOXIDE USP Product Label

CARBON DIOXIDE, USP UN 1013

NLR

Distributed by:

NLR WELDING SUPPLY INC.

501 E. Broadway NLR, AR 72117

(581) 945-0986 www.nlrwelding.com

NON-FLAMMABLE GAS 2

Rx ONBLY. WARNING: Administration of Carbon Dioxide may be hazardous or contraindicated. For use only by or under the supervision of a licensed practioner who is experienced in the use and administration of Carbon Dioxide and is familiar the indications, effects, dosages, methods, and frequency and duration of administration, and with the hazards, contraindications and side effects, and the precautions to be taken.

WARNING: CONTAINS GAS UNDER PRESSURE; MAY EXPLODE IF HEATED. MAY DISPLACE OXYGEN AND CAUSE RAPID SUFFOCATION, MAY CAUSE FROSTBITE. MAY INCREASE RESPIRATION AND HEART RATE. Do not handle until all safety precautions have been read and understood. Avoid breathing gas. Do not get in eyes, on skin, or on clothing. Use and store only outdoors or in a well-ventilated place. Use a backflow preventive device in the piping. Use only with equipment rated for cylinder pressure. Close valve after each use and when empty. Protect from sunlight when ambient temperature exceeds 52°C (125°F). Read and follow the Safety Data Sheet (SDS) before use. FIRST AID: IF INHALED: Remove person to fresh air and keep comfortable for breathing. Get medical advice/attention. IF ON SKIN: Thaw frosted parts with lukewarm water. Do not rub affected area. Get immediate medical advice/attention.

CAS: 124-38-9 DO NOT REMOVE THIS PRODUCT LABEL